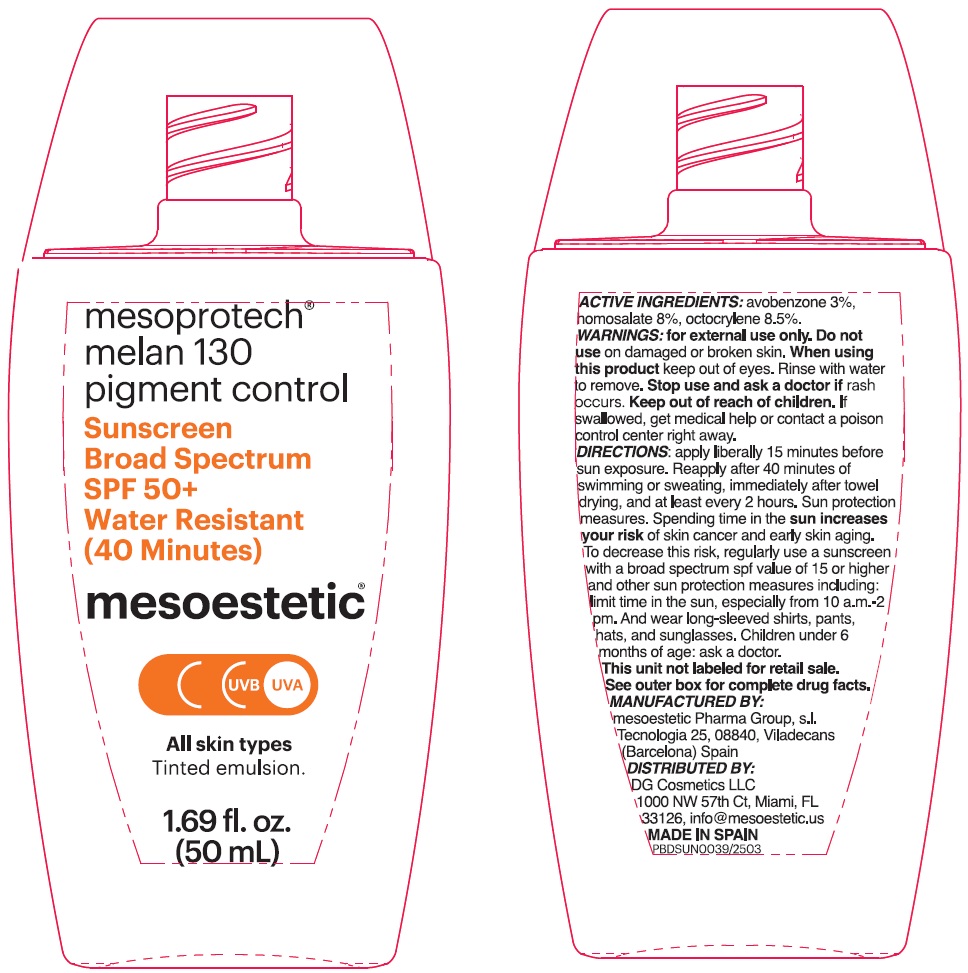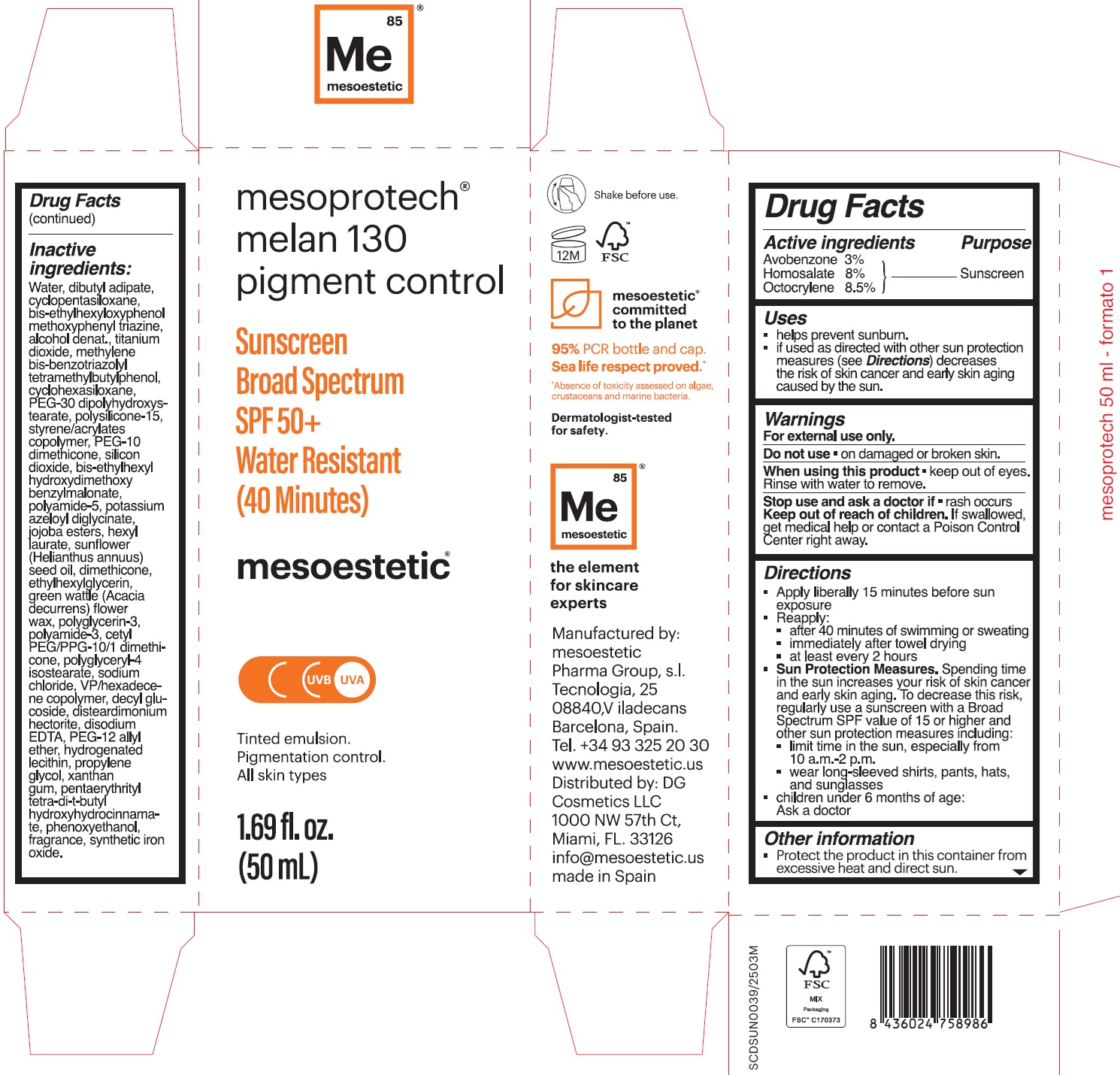 DRUG LABEL: Mesoestetic Mesoprotech Melan 130 Pigment Control
NDC: 76450-001 | Form: EMULSION
Manufacturer: MESOESTETIC PHARMA GROUP SL
Category: otc | Type: HUMAN OTC DRUG LABEL
Date: 20250401

ACTIVE INGREDIENTS: AVOBENZONE 30 mg/1 mL; HOMOSALATE 80 mg/1 mL; OCTOCRYLENE 85 mg/1 mL
INACTIVE INGREDIENTS: WATER; DIBUTYL ADIPATE; CYCLOMETHICONE 5; BEMOTRIZINOL; ALCOHOL; TITANIUM DIOXIDE; BISOCTRIZOLE; CYCLOMETHICONE 6; PEG-30 DIPOLYHYDROXYSTEARATE (4000 MW); POLYSILICONE-15; SILICON DIOXIDE; BIS-ETHYLHEXYL HYDROXYDIMETHOXY BENZYLMALONATE; POLYAMIDE-5; POTASSIUM AZELOYL DIGLYCINATE; HEXYL LAURATE; SUNFLOWER OIL; DIMETHICONE; ETHYLHEXYLGLYCERIN; ACACIA DECURRENS FLOWER WAX; POLYGLYCERIN-3; POLYGLYCERYL-4 ISOSTEARATE; SODIUM CHLORIDE; VINYLPYRROLIDONE/HEXADECENE COPOLYMER; DECYL GLUCOSIDE; DISTEARDIMONIUM HECTORITE; EDETATE DISODIUM; PROPYLENE GLYCOL; XANTHAN GUM; PENTAERYTHRITOL TETRAKIS(3-(3,5-DI-TERT-BUTYL-4-HYDROXYPHENYL)PROPIONATE); PHENOXYETHANOL

Mesoestetic Mesoprotech Melan 130 Pigment Control Sunscreen SPF 50+

Active ingredients

Avobenzone 3%

Homosalate 8%

Octocrylene 8.5%

Purpose

Sunscreen

Uses

- helps prevent sunburn.
- if used as directed with other sun protection measures (see Directions) decreases the risk of skin cancer and early skin aging caused by the sun.

Warnings

For external use only.

Do not use

- on damaged or broken skin.

When using this product

- keep out of eyes. Rinse with water to remove.

Stop use and ask a doctor if

- rash occurs

Keep out of reach of children.

If swallowed, get medical help or contact a Poison Control Center right away.

Directions

- Apply liberally 15 minutes before sun exposure
- Reapply:
- after 40 minutes of swimming or sweating
- immediately after towel drying
- at least every 2 hours
- Sun Protection Measures.Spending time in the sun increases your risk of skin cancer and early skin aging. To decrease this risk, regularly use a sunscreen with a Broad Spectrum SPF value of 15 or higher and other sun protection measures including:
- limit time in the sun, especially from 10 a.m. -2 p.m.
- wear long-sleeved shirts, pants, hats, and sunglasses
- children under 6 months of age: Ask a doctor

Other information

- Protect the product in this container from excessive heat and direct sun.

Inactive ingredients:

Water, dibutyl adipate, cyclopentasiloxane, bis-ethylhexyloxyphenol methoxyphenyl triazine, alcohol denat., titanium dioxide, methylene bis-benzotriazolyl tetramethylbutylphenol, cyclohexasiloxane, PEG-30 dipolyhydroxystearate, polysilicone-15, styrene/acrylates copolymer, PEG-10 dimethicone, silicon dioxide, bis-ethylhexyl hydroxydimethoxy benzylmalonate, polyamide-5, potassium azeloyl diglycinate, jojoba esters, hexyl laurate, sunflower (Helianthus annuus) seed oil, dimethicone, ethylhexylglycerin, green wattle (Acacia decurrens) flower wax, polyglycerin-3, polyamide-3, cetyl PEG/PPG-10/1 dimethicone, polyglyceryl-4 isostearate, sodium chloride, VP/hexadecane copolymer, decyl glucoside, disteardimonium hectorite, disodium EDTA, PEG-12 alkyl ether, hydrogenated lecithin, propylene glycol, xanthan gum, pentaerythrityl tetra-di-t-butyl hydroxyhydrocinnamate, phenoxyethanol, fragrance, synthetic iron oxide.